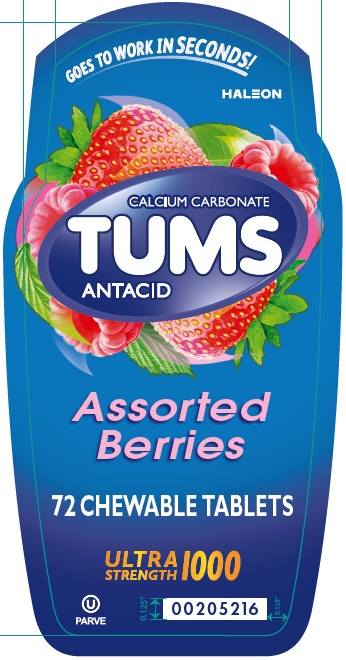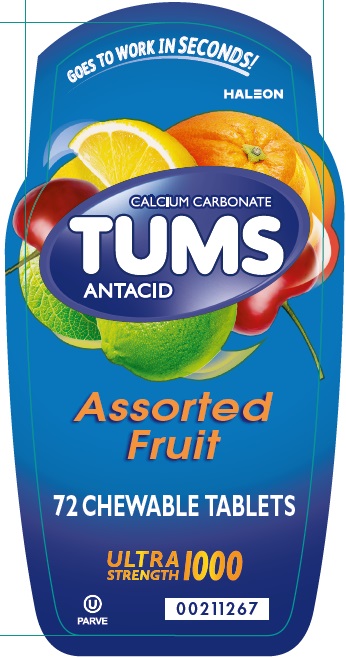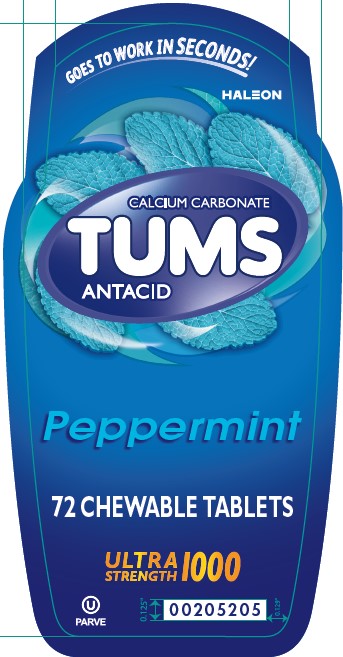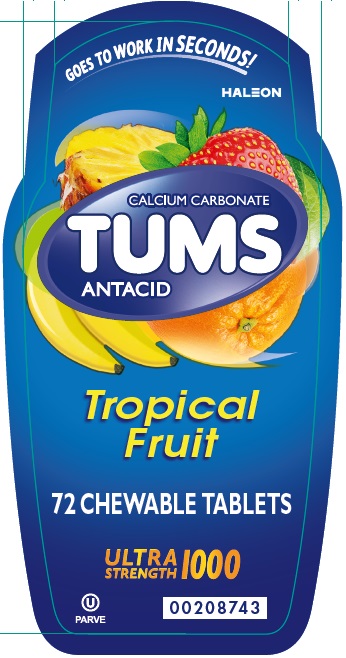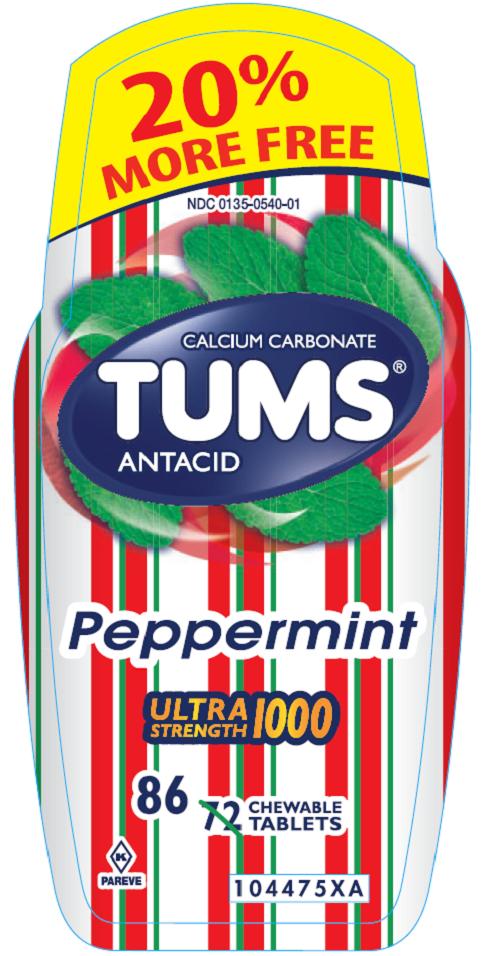 DRUG LABEL: TUMS

NDC: 0135-0118 | Form: TABLET, CHEWABLE
Manufacturer: Haleon US Holdings LLC
Category: otc | Type: HUMAN OTC DRUG LABEL
Date: 20250522

ACTIVE INGREDIENTS: CALCIUM CARBONATE 1000 mg/1 1
INACTIVE INGREDIENTS: SUCROSE; STARCH, CORN; TALC; MINERAL OIL; ADIPIC ACID; SODIUM POLYMETAPHOSPHATE; FD&C RED NO. 40; FD&C YELLOW NO. 6; FD&C YELLOW NO. 5; FD&C BLUE NO. 1; ALUMINUM OXIDE

Drug Facts

Active ingredient (per tablet)

Calcium Carbonate 1000 mg

Purpose

Antacid

Uses

relieves

- heartburn
- acid indigestion
- sour stomach
- upset stomach associated with these symptoms

Warnings

Ask a doctor or pharmacist before use if you are

presently taking a prescription drug. Antacids may interact with certain prescription drugs.

When using this product

- do not take more than 7 tablets in 24 hours
- if pregnant do not take more than 5 tablets in 24 hours
- do not use the maximum dosage for more than 2 weeks, except under the advice and supervision of a doctor

Directions

- adults and children 12 years of age and over:chew 2-3 tablets as symptoms occur, or as directed by a doctor. Chew or crush tablets completely before swallowing.
- do not take for symptoms that persist for more than 2 weeks unless advised by a doctor

Other information

- each tablet contains:elemental calcium 410 mg, magnesium 5 mg, sodium 2mg
- store below 30oC (86oF)

Other information– (Tropical Fruit and Assorted Fruit)

- each tablet contains:elemental calcium 410 mg, magnesium 5 mg, sodium 2mg
- store below 30oC (86oF)
- contains FD&C Yellow No. 5 (tartrazine) as a color additive

Inactive ingredients (Assorted Fruit)

adipic acid, corn starch, FD&C blue #1 lake, FD&C red #40 lake, FD&C yellow #5 (tartrazine) lake, FD&C yellow #6 lake, flavors, mineral oil, sodium polyphosphate, sucrose, talc

Inactive ingredients (Assorted Tropical Fruit)

corn starch, FD&C red #40 lake, FD&C yellow #5 (tartrazine) lake, FD&C yellow #6 lake, flavors, mineral oil, sodium polyphosphate, sucrose, talc

Inactive ingredients (Assorted Berry)

adipic acid, corn starch, FD&C blue #1 lake, FD&C red #40 lake, flavors, mineral oil, sodium polyphosphate, sucrose, talc

Inactive ingredient (Peppermint)

corn starch, flavor, mineral oil, sodium polyphosphate, sucrose, talc

Inactive ingredients (Peppermint Tri-Color)

corn starch, FD&C blue #1 lake, FD&C red #40 lake, FD&C yellow #5 (tartrazine) lake, flavor, mineral oil, sodium polyphosphate, sucrose, talc

Questions?

1-800-897-7535

Safety sealed- Do not use if printed inner seal beneath cap is missing or broken.

Gluten-Free

Principal Display Panel – Assorted Fruit

GOES TO WORK IN SECONDS!

CALCIUM CARBONATE

TUMS

ANTACID

Assorted Fruit

72 CHEWABLE TABLETS

ULTRASTRENGTH 1000

PAREVE

Principal Display Panel – Tropical Fruit

GOES TO WORK IN SECONDS!

CALCIUM CARBONATE

TUMS

ANTACID

Tropical Fruit

72 CHEWABLE TABLETS

ULTRASTRENGTH 1000

PAREVE

Principal Display Panel – Assorted Berries

GOES TO WORK IN SECONDS!

CALCIUM CARBONATE

TUMS

ANTACID

Assorted Berries

72 CHEWABLE TABLETS

ULTRASTRENGTH 1000

PAREVE

Principal Display Panel - Peppermint

GOES TO WORK IN SECONDS!

CALCIUM CARBONATE

TUMS

ANTACID

Peppermint

72 CHEWABLE TABLETS

ULTRASTRENGTH 1000

PAREVE

Principal Display Panel – Peppermint (Tricolor)

NDC 0135-0540-01

TUMS®

ANTACID

CALICUM CARBONATE

PEPPERMINT

ULTRASTRENGTH 1000

86CHEWABLE TABLETS

20% MORE FREE

PAREVE